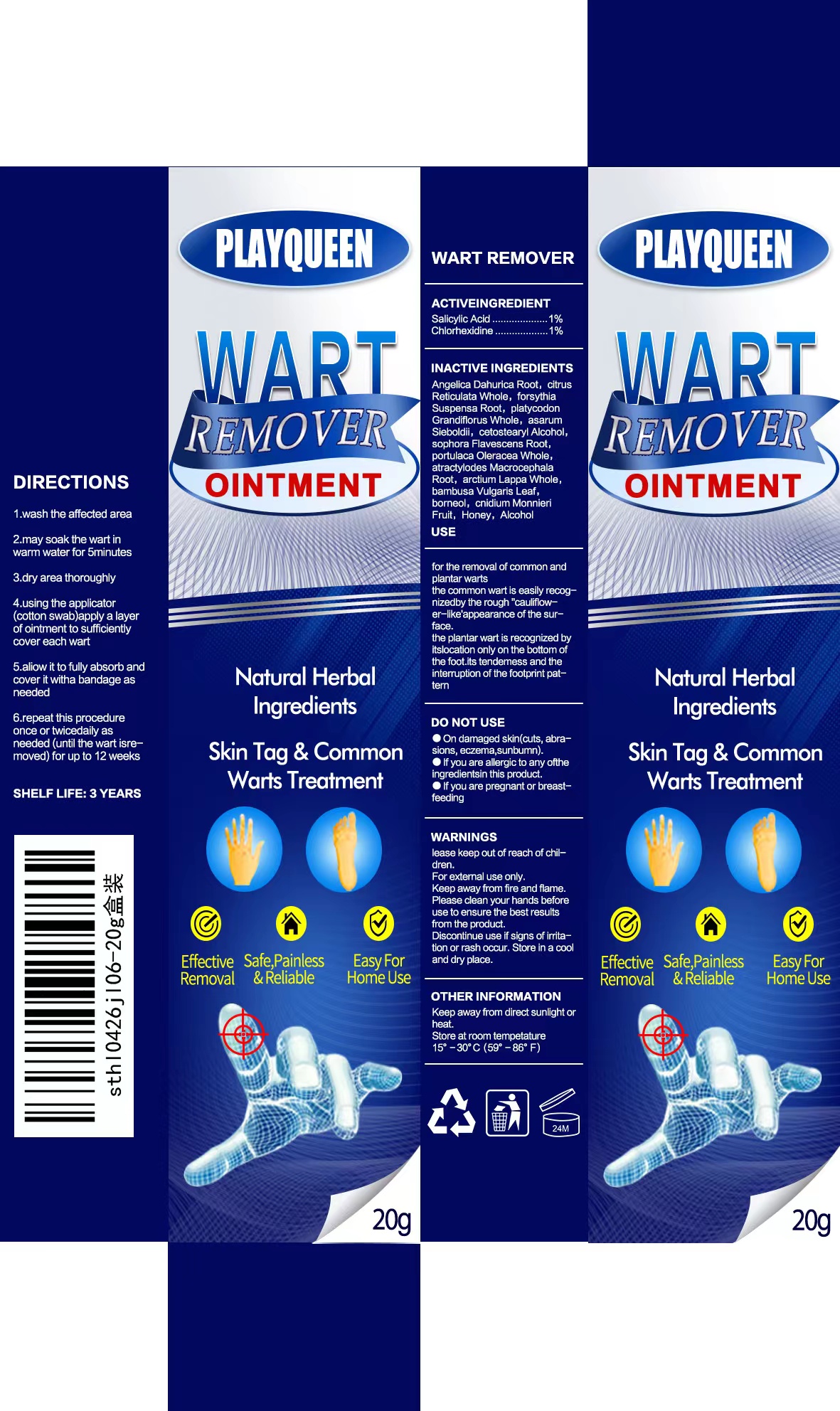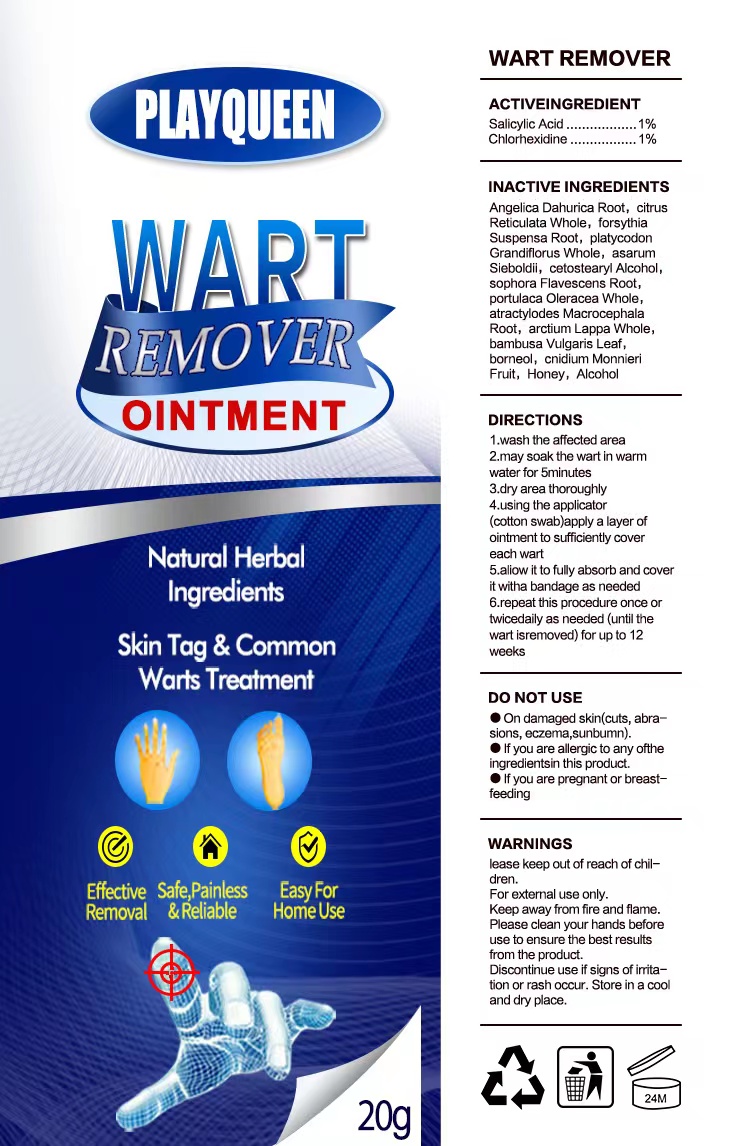 DRUG LABEL: Wart Remover Ointmen t
NDC: 84288-001 | Form: OINTMENT
Manufacturer: Dongkou County Hecheng Network Technology Co., Ltd.
Category: otc | Type: HUMAN OTC DRUG LABEL
Date: 20240510

ACTIVE INGREDIENTS: SALICYLIC ACID 1 g/100 g; CHLORHEXIDINE 1 g/100 g
INACTIVE INGREDIENTS: FORSYTHIA SUSPENSA ROOT; ASARUM SIEBOLDII; BAMBUSA VULGARIS LEAF; BORNEOL; PLATYCODON GRANDIFLORUS WHOLE; CETOSTEARYL ALCOHOL; CNIDIUM MONNIERI FRUIT; ALCOHOL; CITRUS RETICULATA WHOLE; ATRACTYLODES MACROCEPHALA ROOT; ANGELICA DAHURICA ROOT; PORTULACA OLERACEA WHOLE; ARCTIUM LAPPA WHOLE; SOPHORA FLAVESCENS ROOT; HONEY

Wart Remover Ointment

Wart Remover Ointment

ACTIVE INGREDIENT

SALICYLIC ACID 1%
CHLORHEXIDINE 1%

PURPOSE

WART REMOVER

INDICATIONS AND USAGE

for the removal of common andplantar warts.
the common wart is easily recog-nizedby the rough "cauliflow-er-like'appearance of the sur-face.
the plantar wart is recognized byitslocation only on the bottom ofthe foot.its tendemess and theinterruption of the footprint pat-tern.

WARNINGS

For external use only.
Keep away from fire and flame.Please clean your hands beforeuse to ensure the best resultsfrom the product.

DO NOT USE

On damaged skin(cuts, abra-sions, eczema,sunbumn).
If you are allergic to any oftheingredientsin this product.
If you are pregnant or breast-feeding

WHEN USING

1.wash the affected area.
2.may soak the wart in warmwater for 5minutes.
3.dry area thoroughly.
4.using the applicator(cotton swab)apply a layer ofointment to sufficiently covereach wart.
5.aliow it to fully absorb and coverit witha bandage as needed.
6.repeat this procedure once ortwicedaily as needed (until thewart isremoved) for up to 12weeks.

STOP USE

Discontinue use if signs of irrita-tion or rash occur.

lease keep out of reach of chil-dren.

DOSAGE AND ADMINISTRATION

1.wash the affected area.
2.may soak the wart in warmwater for 5minutes.
3.dry area thoroughly.
4.using the applicator(cotton swab)apply a layer ofointment to sufficiently covereach wart.
5.aliow it to fully absorb and coverit witha bandage as needed.
6.repeat this procedure once ortwicedaily as needed (until thewart isremoved) for up to 12weeks.

STORAGE AND HANDLING

Store in a cooland dry place.

INACTIVE INGREDIENT

ANGELICA DAHURICA ROOT
CITRUS RETICULATA WHOLE
FORSYTHIA SUSPENSA ROOT
PLATYCODON GRANDIFLORUS WHOLE
ASARUM SIEBOLDII
CETOSTEARYL ALCOHOL
SOPHORA FLAVESCENS ROOT
PORTULACA OLERACEA WHOLE
ATRACTYLODES MACROCEPHALA ROOT
ARCTIUM LAPPA WHOLE
BAMBUSA VULGARIS LEAF
BORNEOL
CNIDIUM MONNIERI FRUIT
HONEY
ALCOHOL